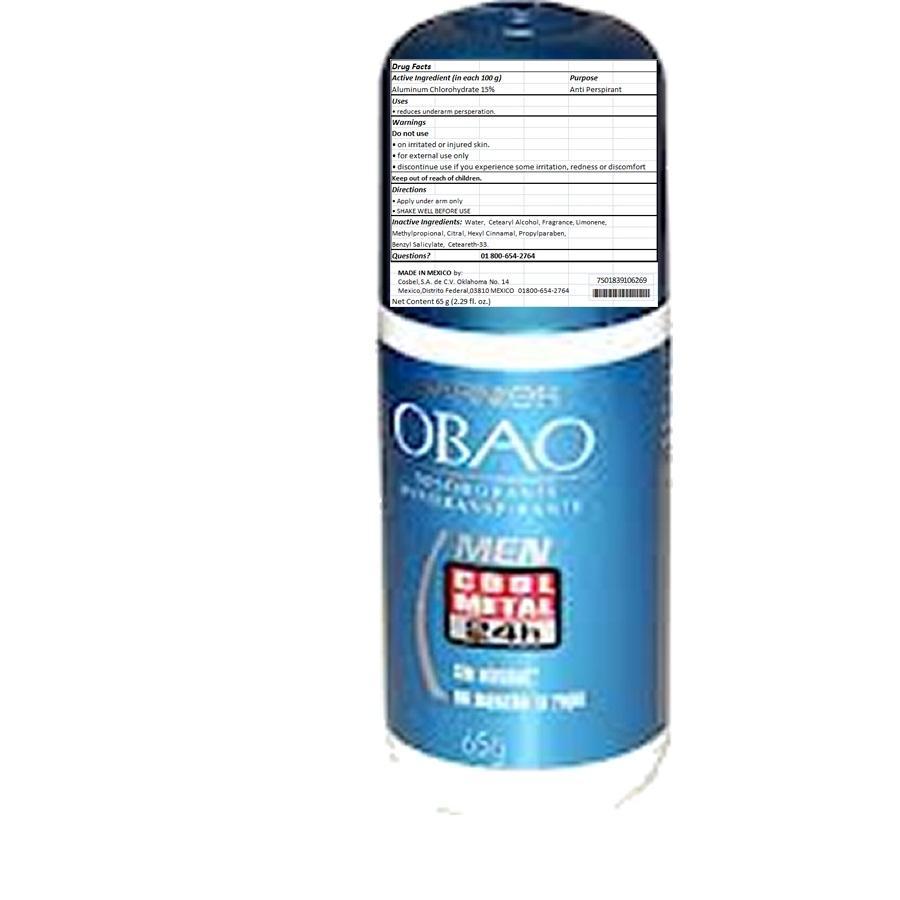 DRUG LABEL: Obao
NDC: 51769-125 | Form: STICK
Manufacturer: ALL NATURAL DYNAMICS
Category: otc | Type: HUMAN OTC DRUG LABEL
Date: 20130816

ACTIVE INGREDIENTS: Aluminum Chlorohydrate 15 g/100 g
INACTIVE INGREDIENTS: Water; CETOSTEARYL ALCOHOL; LINALOOL, DL-; METHYL PROPIONATE; Citral; .ALPHA.-HEXYLCINNAMALDEHYDE; Propylparaben; Benzyl Salicylate; Ceteareth-33

OBAO Coll Metal

Warnings:

For External Use Only. Do Not Apply On Irritated Or Injured Skin. Discontinue Use If You Experience Some Irritation, Redness Or Discomfort.

Active Ingredient:

Aluminum Chlorohydrate 15%

Purpose

Anti Perspirant

Keep Out Of The Reach Of Children

USE:

reduces underarm persperation

Directions:

Apply under arm only.

SHAKE WELL BEFORE USE.

Inactive Ingredients:

Water, Cetearyl Alcohol, Fragrance, Limonene,

Methylpropional, Citral, Hexyl Cinnamal, Propylparaben,

Benzyl Salicylate, Ceteareth-33.